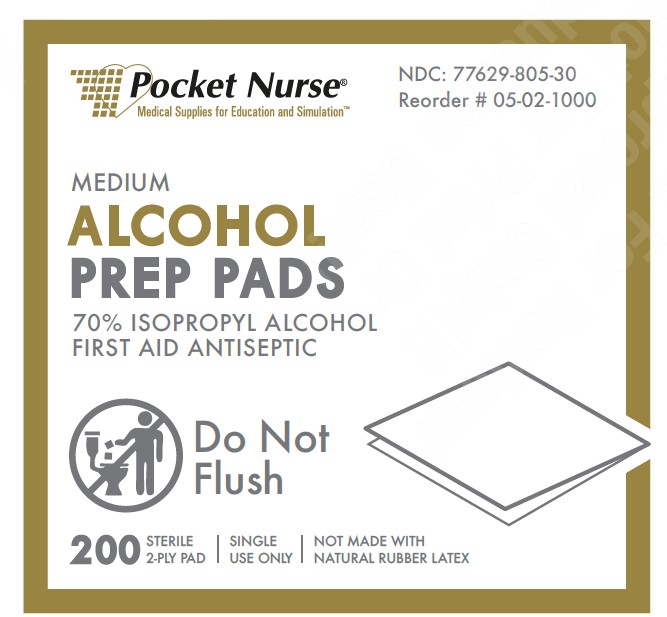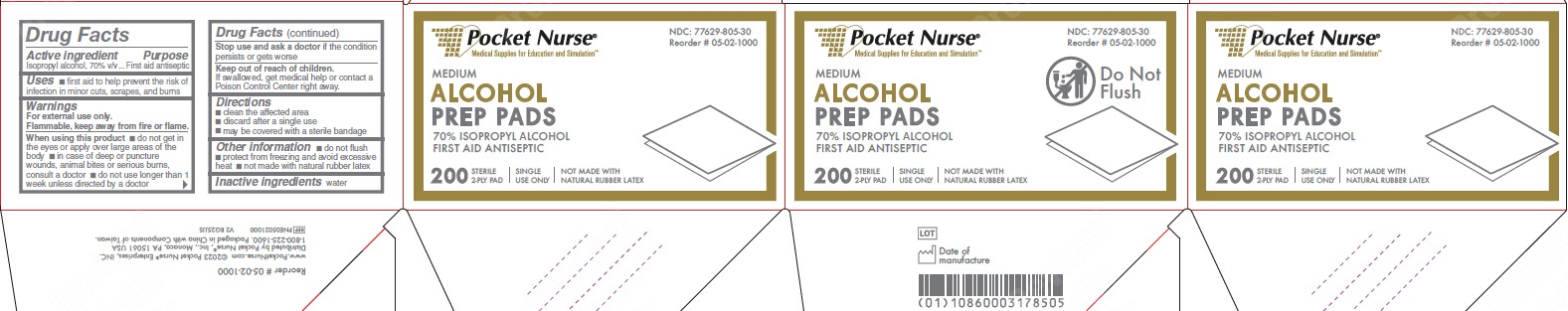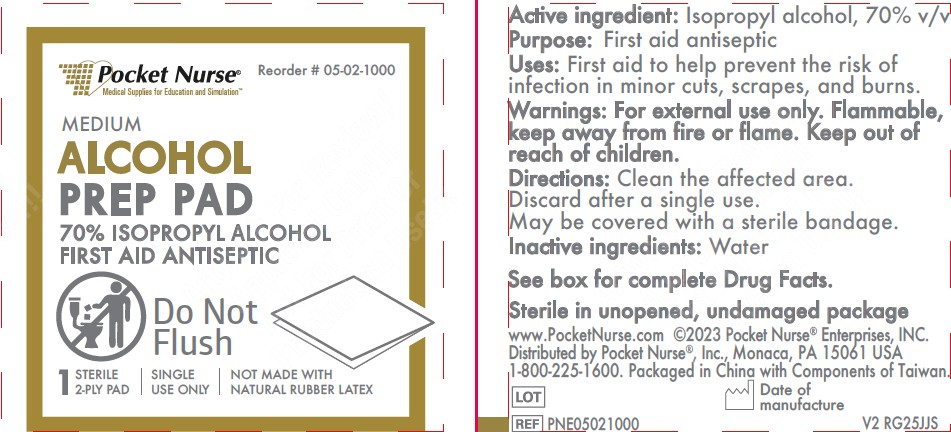 DRUG LABEL: Pocket Nurse
NDC: 77629-805 | Form: SWAB
Manufacturer: Pocket Nurse Enterprises, LLC
Category: otc | Type: HUMAN OTC DRUG LABEL
Date: 20251106

ACTIVE INGREDIENTS: ISOPROPYL ALCOHOL 70 mL/100 mL
INACTIVE INGREDIENTS: WATER

77629-805 Pocket Nurse IPA Prep Pad

Active Ingredient

Isopropyl alcohol, 70% v/v

Purpose

First aid antiseptic

Uses

- first aid to help prevent the risk of infection in minor cuts, scrapes, and burns

Warnings

For external use only.

Flammable, keep away from fire or flame.

When using this product

- do not get in the eyes or apply over large areas of the body
- in case of deep or puncture wounds, animal bites, or serious burns, consult a doctor
- do not use longer than 1 week unless directed by a doctor

Stop use and ask a doctor

if the condition persists or gets worse

Keep out of reach of children.

If swallowed, get medical help or contact a Poison Control Center right away.

Directions

- clean the affected area
- discard after a single use
- may be covered with a sterile bandage

Other information

- do not flush
- protect from freezing and avoid excessive heat
- not made with natural rubber latex

Inactive Ingredients

water

Manufacturer Information

www.PocketNurse.com

©2023 Pocket Nurse® Enterprises, INC.

Distributed by Pocket Nurse®, Inc.,

Monaco, PA 15061 USA

1-800-225-1600.

Packaged in China with Components of Taiwan

REF: PNE05021000